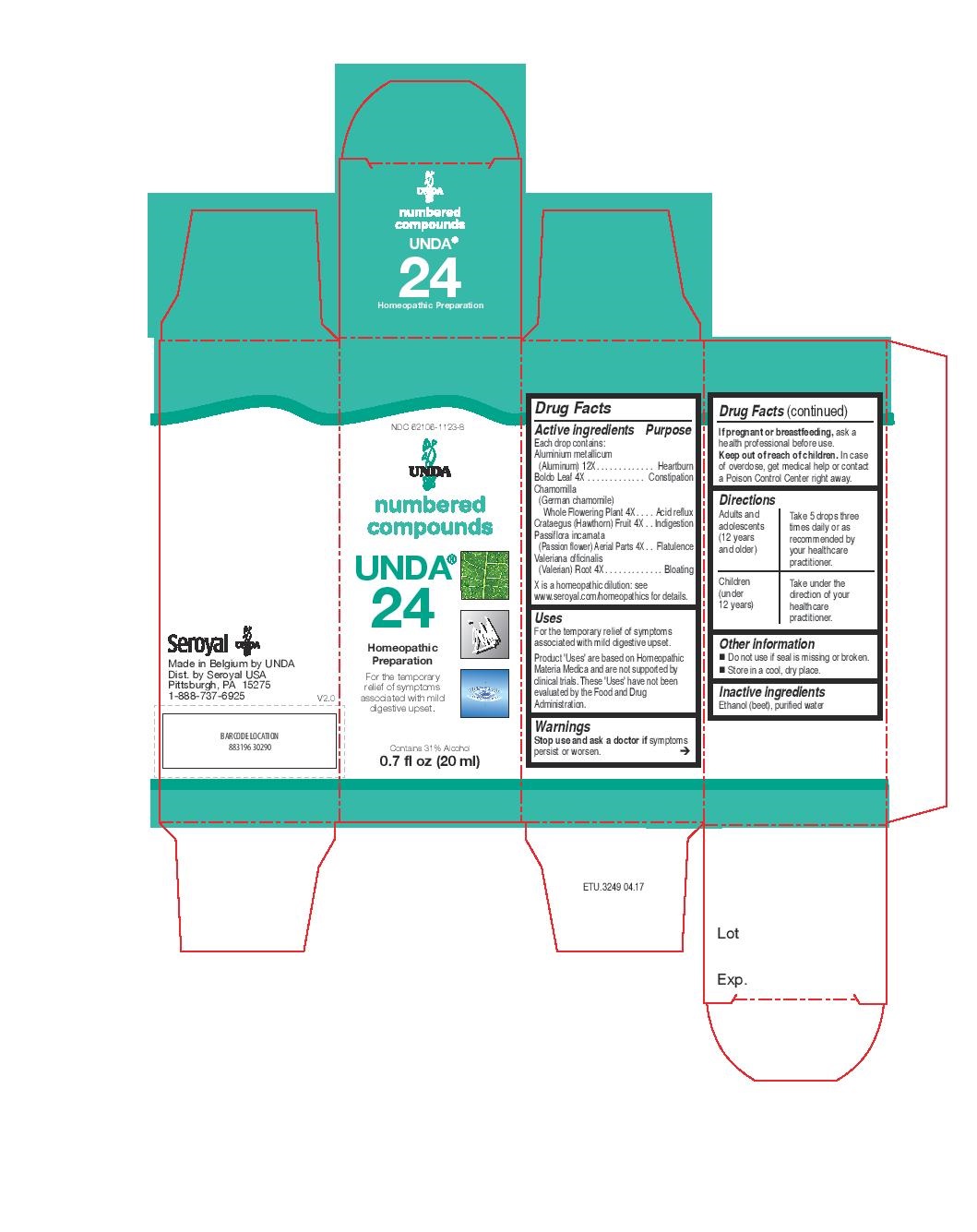 DRUG LABEL: Unda 24
NDC: 62106-1123 | Form: LIQUID
Manufacturer: Seroyal USA
Category: homeopathic | Type: HUMAN OTC DRUG LABEL
Date: 20221109

ACTIVE INGREDIENTS: PEUMUS BOLDUS LEAF 4 [hp_X]/20 mL; CRATAEGUS FRUIT 4 [hp_X]/20 mL; PASSIFLORA INCARNATA FLOWERING TOP 4 [hp_X]/20 mL; VALERIAN 4 [hp_X]/20 mL; MATRICARIA RECUTITA 4 [hp_X]/20 mL; ALUMINUM 12 [hp_X]/20 mL
INACTIVE INGREDIENTS: WATER; ALCOHOL

UNDA 24

Active ingredients
Each drop contains:
Aluminium metallicum (Aluminum) 12X
Boldo Leaf 4X
Chamomilla (German chamomile) Whole Flowering Plant 4X
Crataegus (Hawthorn) Fruit 4X
Passiflora incarnata (Passion flower) Aerial Parts 4X
Valeriana officinalis (Valerian) Root 4X

Uses
For the temporary relief of symptoms associated with mild digestive upset.

Warnings
Stop use and ask a doctor if symptoms persist or worsen.
If pregnant or breastfeeding, ask a health professional before use.

Keep out of reach of children.

In case of overdose, get medical help or contact a
Poison Control Center right away.

PREGNANCY OR BREAST FEEDING

If pregnant or breastfeeding, ask a health professional before use.

Keep out of reach of children.

OVERDOSAGE

In case of overdose, get medical help or contact a

Poison Control Center right away.

Stop use and ask a doctor if symptoms persist or worsen.

Inactive Ingredients:

Ethanol (beet),
purified water

Directions
Adults and adolescents (12 years and older)

Take 5 drops three times daily or as recommended by your healthcare practitioner.

Children (under 12 years)

Take under the direction of your healthcare practitioner.

Uses
For the temporary relief of symptoms associated with mild digestive upset.

Directions
Adults and adolescents (12 years and older)

Take 5 drops three times daily or as recommended by your healthcare practitioner.

Children (under 12 years)

Take under the direction of your healthcare practitioner.

PACKAGE LABEL

NDC 62106-1123-8

UNDA

numbered compounds

UNDA 24

Homeopathic Preparation

For the temporary relief of symptoms
associated with mild digestive upset.

Contains 31% Alcohol
0.7 fl oz (20 ml)